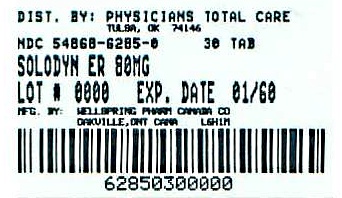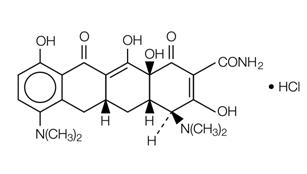 DRUG LABEL: Solodyn
NDC: 54868-6285 | Form: TABLET, FILM COATED, EXTENDED RELEASE
Manufacturer: Physicians Total Care, Inc.
Category: prescription | Type: HUMAN PRESCRIPTION DRUG LABEL
Date: 20110404

ACTIVE INGREDIENTS: minocycline hydrochloride 80 mg/1 1
INACTIVE INGREDIENTS: hypromellose 2910 (50 mpa.s); lactose monohydrate; polyethylene glycol 3350; FD&C Blue No. 2; FD&C Red No. 40; titanium dioxide; triacetin; FD&C Yellow No. 6

HIGHLIGHTS OF PRESCRIBING INFORMATION

These highlights do not include all the information needed to use SOLODYN safely and effectively. See full prescribing information for SOLODYN.
SOLODYN®
(minocycline HCl) Extended Release Tablets for oral use
Initial U.S. Approval: 1971

1 INDICATIONS AND USAGE

SOLODYN is a tetracycline-class drug indicated to treat only inflammatory lesions of non-nodular moderate to severe acne vulgaris in patients 12 years of age and older. (1)

2 DOSAGE AND ADMINISTRATION

The recommended dosage of SOLODYN is approximately 1 mg/kg once daily for 12 weeks. (2)

3 DOSAGE FORMS AND STRENGTHS

Extended release tablets: 45, 55, 65, 80, 90, 105, 115, and 135 mg (3)

4 CONTRAINDICATIONS

This drug is contraindicated in persons who have shown hypersensitivity to any of the tetracyclines. (4)

5 WARNINGS AND PRECAUTIONS

- The use of SOLODYN during tooth development (last half of pregnancy, infancy, and childhood up to the age of 8 years) may cause permanent discoloration of the teeth (yellow-gray-brown). (5.1)
- If pseudomembranous colitis occurs, discontinue SOLODYN. (5.2)
- If liver injury is suspected, discontinue SOLODYN. (5.3)
- If renal impairment exists, SOLODYN doses may need to be adjusted to avoid excessive systemic accumulations of the drug and possible liver toxicity. (5.4)
- Minocycline may cause central nervous system side effects including light-headedness, dizziness, or vertigo. Advise patients. (5.5)
- Minocycline may cause pseudotumor cerebri (benign intracranial hypertension) in adults and adolescents. Discontinue SOLODYN if symptoms occur. (5.6)
- Minocycline has been associated with autoimmune syndromes; discontinue SOLODYN immediately if symptoms occur. (5.7)
- Minocycline has been associated with anaphylaxis, serious skin reactions, erythema multiforme, and DRESS syndrome. Discontinue SOLODYN immediately if symptoms occur. (5.9)

6 ADVERSE REACTIONS

The most commonly observed adverse reactions (incidence ≥ 5%) are headache, fatigue, dizziness, and pruritus. (6.1)

To report SUSPECTED ADVERSE REACTIONS, contact Medicis, The Dermatology Company at 1-800-900-6389 or FDA at 1-800-FDA-1088 or www.fda.gov/medwatch.

7 DRUG INTERACTIONS

- Patients who are on anticoagulant therapy may require downward adjustment of their anticoagulant dosage. (7.1)
- The concurrent use of tetracycline and methoxyflurane has been reported to result in fatal renal toxicity. (7.3)
- To avoid contraceptive failure, female patients are advised to use a second form of contraceptive during treatment with minocycline. (7.5)

8 USE IN SPECIFIC POPULATIONS

- Minocycline like other tetracycline-class drugs can cause fetal harm when administered to a pregnant woman. (5.1, 8.1)
- The use of drugs of the tetracycline class during tooth development may cause permanent discoloration of teeth. (5.1, 8.4)

FULL PRESCRIBING INFORMATION

1 INDICATIONS AND USAGE

1.1 Indication

SOLODYN is indicated to treat only inflammatory lesions of non-nodular moderate to severe acne vulgaris in patients 12 years of age and older.

1.2 Limitations of Use

SOLODYN did not demonstrate any effect on non-inflammatory acne lesions. Safety of SOLODYN has not been established beyond 12 weeks of use. This formulation of minocycline has not been evaluated in the treatment of infections [see Clinical Studies (14)].

To reduce the development of drug-resistant bacteria as well as to maintain the effectiveness of other antibacterial drugs, SOLODYN should be used only as indicated [see Warnings and Precautions (5.11)].

2 DOSAGE AND ADMINISTRATION

The recommended dosage of SOLODYN is approximately 1 mg/kg once daily for 12 weeks. Higher doses have not shown to be of additional benefit in the treatment of inflammatory lesions of acne, and may be associated with more acute vestibular side effects.

The following table shows tablet strength and body weight to achieve approximately 1 mg/kg.

Table 1: Dosing Table for SOLODYN
Patient's Weight (lbs.) | Patient's Weight (kg) | Tablet Strength (mg) | Actual mg/kg Dose
99 – 109 | 45 – 49 | 45 | 1 – 0.92
110 – 131 | 50 – 59 | 55 | 1.10 – 0.93
132 – 157 | 60 – 71 | 65 | 1.08 – 0.92
158 – 186 | 72 – 84 | 80 | 1.11 – 0.95
187 – 212 | 85 – 96 | 90 | 1.06 – 0.94
213 – 243 | 97 – 110 | 105 | 1.08 – 0.95
244 – 276 | 111 – 125 | 115 | 1.04 – 0.92
277 – 300 | 126 – 136 | 135 | 1.07 – 0.99

SOLODYN Tablets may be taken with or without food [see Clinical Pharmacology (12)]. Ingestion of food along with SOLODYN may help reduce the risk of esophageal irritation and ulceration.

In patients with renal impairment, the total dosage should be decreased by either reducing the recommended individual doses and/or by extending the time intervals between doses [see Warnings and Precautions (5.4)].

3 DOSAGE FORMS AND STRENGTHS

- 45 mg extended release tablets: gray, unscored, coated, and debossed with "DYN-045" on one side.
- 55 mg extended release tablets: pink, unscored, coated, and debossed with "DYN-055" on one side.
- 65 mg extended release tablets: blue, unscored, coated, and debossed with "DYN-065" on one side.
- 80 mg extended release tablets: gray, unscored, coated, and debossed with "DYN-080" on one side.
- 90 mg extended release tablets: yellow, unscored, coated, and debossed with "DYN-090" on one side.
- 105 mg extended release tablets: purple, unscored, coated, and debossed with "DYN-105" on one side.
- 115 mg extended release tablets: green, unscored, coated, and debossed with "DYN-115" on one side.
- 135 mg extended release tablets: pink (orange-brown), unscored, coated, and debossed with "DYN-135" on one side.

4 CONTRAINDICATIONS

This drug is contraindicated in persons who have shown hypersensitivity to any of the tetracyclines.

5 WARNINGS AND PRECAUTIONS

5.1 Teratogenic Effects

1. MINOCYCLINE, LIKE OTHER TETRACYCLINE-CLASS DRUGS, CAN CAUSE FETAL HARM WHEN ADMINISTERED TO A PREGNANT WOMAN. IF ANY TETRACYCLINE IS USED DURING PREGNANCY OR IF THE PATIENT BECOMES PREGNANT WHILE TAKING THESE DRUGS, THE PATIENT SHOULD BE APPRISED OF THE POTENTIAL HAZARD TO THE FETUS.
  SOLODYN should not be used during pregnancy or by individuals of either gender who are attempting to conceive a child [see Nonclinical Toxicology (13.1) & Use in Specific Populations (8.1)].
2. THE USE OF DRUGS OF THE TETRACYCLINE CLASS DURING TOOTH DEVELOPMENT (LAST HALF OF PREGNANCY, INFANCY, AND CHILDHOOD UP TO THE AGE OF 8 YEARS) MAY CAUSE PERMANENT DISCOLORATION OF THE TEETH (YELLOW-GRAY-BROWN).
  This adverse reaction is more common during long-term use of the drug but has been observed following repeated short-term courses. Enamel hypoplasia has also been reported. TETRACYCLINE DRUGS, THEREFORE, SHOULD NOT BE USED DURING TOOTH DEVELOPMENT.
3. All tetracyclines form a stable calcium complex in any bone-forming tissue. A decrease in fibula growth rate has been observed in premature human infants given oral tetracycline in doses of 25 mg/kg every 6 hours. This reaction was shown to be reversible when the drug was discontinued.
  Results of animal studies indicate that tetracyclines cross the placenta, are found in fetal tissues, and can cause retardation of skeletal development on the developing fetus. Evidence of embryotoxicity has been noted in animals treated early in pregnancy [see Use in Specific Populations (8.1)].

5.2 Pseudomembranous Colitis

Pseudomembranous colitis has been reported with nearly all antibacterial agents and may range from mild to life-threatening. Therefore, it is important to consider this diagnosis in patients who present with diarrhea subsequent to the administration of antibacterial agents.

Treatment with antibacterial agents alters the normal flora of the colon and may permit overgrowth of clostridia. Studies indicate that a toxin produced by Clostridium difficile is a primary cause of "antibiotic-associated colitis".

After the diagnosis of pseudomembranous colitis has been established, therapeutic measures should be initiated. Mild cases of pseudomembranous colitis usually respond to discontinuation of the drug alone. In moderate to severe cases, consideration should be given to management with fluids and electrolytes, protein supplementation, and treatment with an antibacterial drug clinically effective against Clostridium difficile colitis.

5.3 Hepatotoxicity

Post-marketing cases of serious liver injury, including irreversible drug-induced hepatitis and fulminant hepatic failure (sometimes fatal) have been reported with minocycline use in the treatment of acne.

5.4 Metabolic Effects

The anti-anabolic action of the tetracyclines may cause an increase in BUN. While this is not a problem in those with normal renal function, in patients with significantly impaired function, higher serum levels of tetracycline-class drugs may lead to azotemia, hyperphosphatemia, and acidosis. If renal impairment exists, even usual oral or parenteral doses may lead to excessive systemic accumulations of the drug and possible liver toxicity. Under such conditions, lower than usual total doses are indicated, and if therapy is prolonged, serum level determinations of the drug may be advisable.

5.5 Central Nervous System Effects

Central nervous system side effects including light-headedness, dizziness or vertigo have been reported with minocycline therapy. Patients who experience these symptoms should be cautioned about driving vehicles or using hazardous machinery while on minocycline therapy. These symptoms may disappear during therapy and usually rapidly disappear when the drug is discontinued.

5.6 Benign Intracranial Hypertension

Pseudotumor cerebri (benign intracranial hypertension) in adults and adolescents has been associated with the use of tetracyclines. Minocycline has been reported to cause or precipitate pseudotumor cerebri, the hallmark of which is papilledema. Clinical manifestations include headache and blurred vision. Bulging fontanels have been associated with the use of tetracyclines in infants. Although signs and symptoms of pseudotumor cerebri resolve after discontinuation of treatment, the possibility for permanent sequelae such as visual loss that may be permanent or severe exists. Patients should be questioned for visual disturbances prior to initiation of treatment with tetracyclines. If visual disturbance occurs during treatment, patients should be checked for papilledema. Concomitant use of isotretinoin and minocycline should be avoided because isotretinoin, a systemic retinoid, is also known to cause pseudotumor cerebri.

5.7 Autoimmune Syndromes

Tetracyclines have been associated with the development of autoimmune syndromes. The long-term use of minocycline in the treatment of acne has been associated with drug-induced lupus-like syndrome, autoimmune hepatitis and vasculitis. Sporadic cases of serum sickness have presented shortly after minocycline use. Symptoms may be manifested by fever, rash, arthralgia, and malaise. In symptomatic patients, liver function tests, ANA, CBC, and other appropriate tests should be performed to evaluate the patients. Use of all tetracycline-class drugs should be discontinued immediately.

5.8 Photosensitivity

Photosensitivity manifested by an exaggerated sunburn reaction has been observed in some individuals taking tetracyclines. This has been reported rarely with minocycline. Patients should minimize or avoid exposure to natural or artificial sunlight (tanning beds or UVA/B treatment) while using minocycline. If patients need to be outdoors while using minocycline, they should wear loose-fitting clothes that protect skin from sun exposure and discuss other sun protection measures with their physician.

5.9 Serious Skin/Hypersensitivity Reaction

Cases of anaphylaxis, serious skin reactions (e.g. Stevens Johnson syndrome), erythema multiforme, and drug rash with eosinophilia and systemic symptoms (DRESS) syndrome have been reported postmarketing with minocycline use in patients with acne. DRESS syndrome consists of cutaneous reaction (such as rash or exfoliative dermatitis), eosinophilia, and one or more of the following visceral complications such as: hepatitis, pneumonitis, nephritis, myocarditis, and pericarditis. Fever and lymphadenopathy may be present. In some cases, death has been reported. If this syndrome is recognized, the drug should be discontinued immediately.

5.10 Tissue Hyperpigmentation

Tetracycline-class antibiotics are known to cause hyperpigmentation. Tetracycline therapy may induce hyperpigmentation in many organs, including nails, bone, skin, eyes, thyroid, visceral tissue, oral cavity (teeth, mucosa, alveolar bone), sclerae and heart valves. Skin and oral pigmentation has been reported to occur independently of time or amount of drug administration, whereas other tissue pigmentation has been reported to occur upon prolonged administration. Skin pigmentation includes diffuse pigmentation as well as over sites of scars or injury.

5.11 Development of Drug-Resistant Bacteria

Bacterial resistance to the tetracyclines may develop in patients using SOLODYN, therefore, the susceptibility of bacteria associated with infection should be considered in selecting antimicrobial therapy. Because of the potential for drug-resistant bacteria to develop during the use of SOLODYN, it should be used only as indicated.

5.12 Superinfection

As with other antibiotic preparations, use of SOLODYN may result in overgrowth of nonsusceptible organisms, including fungi. If superinfection occurs, SOLODYN should be discontinued and appropriate therapy instituted.

5.13 Laboratory Monitoring

Periodic laboratory evaluations of organ systems, including hematopoetic renal and hepatic studies should be performed. Appropriate tests for autoimmune syndromes should be performed as indicated.

6 ADVERSE REACTIONS

6.1 Clinical Trial Experience

Because clinical trials are conducted under prescribed conditions, adverse reaction rates observed in the clinical trial may not reflect the rates observed in practice.

The following table summarizes selected adverse reactions reported in clinical trials at a rate of ≥ 1% for SOLODYN.

Table 2: Selected Treatment-Emergent Adverse Reactions in at least 1% of Clinical Trial Subjects
Adverse Reactions | SOLODYN (1 mg/kg) N = 674 (%) | PLACEBO N = 364 (%)
At least one treatment-emergent event | 379 (56) | 197 (54)
Headache | 152 (23) | 83 (23)
Fatigue | 62 (9) | 24 (7)
Dizziness | 59 (9) | 17 (5)
Pruritus | 31 (5) | 16 (4)
Malaise | 26 (4) | 9 (3)
Mood alteration | 17 (3) | 9 (3)
Somnolence | 13 (2) | 3 (1)
Urticaria | 10 (2) | 1 (0)
Tinnitus | 10 (2) | 5 (1)
Arthralgia | 9 (1) | 2 (0)
Vertigo | 8 (1) | 3 (1)
Dry mouth | 7 (1) | 5 (1)
Myalgia | 7 (1) | 4 (1)

6.2 Postmarketing Experience

Adverse reactions that have been reported with minocycline hydrochloride use in a variety of indications include:

Skin and hypersensitivity reactions: fixed drug eruptions, balanitis, erythema multiforme, Stevens-Johnson syndrome, anaphylactoid purpura, photosensitivity, pigmentation of skin and mucous membranes, hypersensitivity reactions, angioneurotic edema, anaphylaxis, DRESS syndrome [see Warnings and Precautions (5.9)].
Autoimmune conditions: polyarthralgia, pericarditis, exacerbation of systemic lupus, pulmonary infiltrates with eosinophilia, transient lupus-like syndrome.
Central nervous system: pseudotumor cerebri, bulging fontanels in infants, decreased hearing.
Endocrine: brown-black microscopic thyroid discoloration, abnormal thyroid function.
Oncology: thyroid cancer.
Oral: glossitis, dysphagia, tooth discoloration.
Gastrointestinal: enterocolitis, pancreatitis, hepatitis, liver failure.
Renal: reversible acute renal failure.
Hematology: hemolytic anemia, thrombocytopenia, eosinophilia.

Preliminary studies suggest that use of minocycline may have deleterious effects on human spermatogenesis [see Nonclinical Toxicology (13.1)].

7 DRUG INTERACTIONS

7.1 Anticoagulants

Because tetracyclines have been shown to depress plasma prothrombin activity, patients who are on anticoagulant therapy may require downward adjustment of their anticoagulant dosage.

7.2 Penicillin

Since bacteriostatic drugs may interfere with the bactericidal action of penicillin, it is advisable to avoid giving tetracycline-class drugs in conjunction with penicillin.

7.3 Methoxyflurane

The concurrent use of tetracycline and methoxyflurane has been reported to result in fatal renal toxicity.

7.4 Antacids and Iron Preparations

Absorption of tetracyclines is impaired by antacids containing aluminum, calcium or magnesium and iron-containing preparations.

7.5 Low Dose Oral Contraceptives

In a multi-center study to evaluate the effect of SOLODYN on low dose oral contraceptives, hormone levels over one menstrual cycle with and without SOLODYN 1 mg/kg once-daily were measured. Based on the results of this trial, minocycline-related changes in estradiol, progestinic hormone, FSH and LH plasma levels, of breakthrough bleeding, or of contraceptive failure, can not be ruled out. To avoid contraceptive failure, female patients are advised to use a second form of contraceptive during treatment with minocycline.

7.6 Drug/Laboratory Test Interactions

False elevations of urinary catecholamine levels may occur due to interference with the fluorescence test.

8 USE IN SPECIFIC POPULATIONS

8.1 Pregnancy

TERATOGENIC EFFECTS

Teratogenic Effects: Pregnancy category D [see Warnings and Precautions (5.1)]

SOLODYN should not be used during pregnancy. If the patient becomes pregnant while taking this drug, the patient should be apprised of the potential hazard to the fetus and stop treatment immediately.

There are no adequate and well-controlled studies on the use of minocycline in pregnant women. Minocycline, like other tetracycline-class drugs, crosses the placenta and may cause fetal harm when administered to a pregnant woman.

Rare spontaneous reports of congenital anomalies including limb reduction have been reported with minocycline use in pregnancy in post-marketing experience. Only limited information is available regarding these reports; therefore, no conclusion on causal association can be established.

Minocycline induced skeletal malformations (bent limb bones) in fetuses when administered to pregnant rats and rabbits in doses of 30 mg/kg/day and 100 mg/kg/day, respectively, (resulting in approximately 3 times and 2 times, respectively, the systemic exposure to minocycline observed in patients as a result of use of SOLODYN). Reduced mean fetal body weight was observed in studies in which minocycline was administered to pregnant rats at a dose of 10 mg/kg/day (which resulted in approximately the same level of systemic exposure to minocycline as that observed in patients who use SOLODYN).

Minocycline was assessed for effects on peri- and post-natal development of rats in a study that involved oral administration to pregnant rats from day 6 of gestation through the period of lactation (postpartum day 20), at dosages of 5, 10, or 50 mg/kg/day. In this study, body weight gain was significantly reduced in pregnant females that received 50 mg/kg/day (resulting in approximately 2.5 times the systemic exposure to minocycline observed in patients as a result of use of SOLODYN). No effects of treatment on the duration of the gestation period or the number of live pups born per litter were observed. Gross external anomalies observed in F1 pups (offspring of animals that received minocycline) included reduced body size, improperly rotated forelimbs, and reduced size of extremities. No effects were observed on the physical development, behavior, learning ability, or reproduction of F1 pups, and there was no effect on gross appearance of F2 pups (offspring of F1 animals).

8.3 Nursing Mothers

Tetracycline-class antibiotics are excreted in human milk. Because of the potential for serious adverse effects on bone and tooth development in nursing infants from the tetracycline-class antibiotics, a decision should be made whether to discontinue nursing or discontinue the drug, taking into account the importance of the drug to the mother [see Warnings and Precautions (5.1)].

8.4 Pediatric Use

SOLODYN is indicated to treat only inflammatory lesions of non-nodular moderate to severe acne vulgaris in patients 12 years and older. Safety and effectiveness in pediatric patients below the age of 12 has not been established.

Use of tetracycline-class antibiotics below the age of 8 is not recommended due to the potential for tooth discoloration [see Warnings and Precautions (5.1)].

8.5 Geriatric Use

Clinical studies of SOLODYN did not include sufficient numbers of subjects aged 65 and over to determine whether they respond differently from younger subjects. Other reported clinical experience has not identified differences in responses between the elderly and younger patients. In general, dose selection for an elderly patient should be cautious, usually starting at the low end of the dosing range, reflecting the greater frequency of decreased hepatic, renal, or cardiac function, and concomitant disease or other drug therapy.

10 OVERDOSAGE

In case of overdosage, discontinue medication, treat symptomatically and institute supportive measures. Minocycline is not removed in significant quantities by hemodialysis or peritoneal dialysis.

11 DESCRIPTION

Minocycline hydrochloride, a semi synthetic derivative of tetracycline, is [4S-(4α,4aα,5aα,12aα)]-4,7-Bis(dimethylamino)-1,4,4a,5,5a,6,11,12a-octahydro-3,10,12,12a-tetrahydroxy-1,11-dioxo-2-naphthacenecarboxamide mono hydrochloride. The structural formula is represented below:

C23H27N3O7•HCl M. W. 493.95

SOLODYN Tablets for oral administration contain minocycline hydrochloride USP equivalent to 45 mg, 55 mg, 65 mg, 80 mg, 90 mg, 105 mg, 115 mg, or 135 mg of minocycline. In addition, 45 mg, 55 mg, 65 mg, 80 mg, 90 mg, 105 mg, 115 mg, and 135 mg tablets contain the following inactive ingredients: lactose monohydrate NF, hypromellose type 2910 USP, magnesium stearate NF, colloidal silicon dioxide NF, and carnauba wax NF. The 45 mg tablets also contain Opadry II Gray which contains: lactose monohydrate NF, hypromellose type 2910 USP, titanium dioxide USP, triacetin USP, and iron oxide black JPE. The 55 mg tablets also contain Opadry II Pink which contains: hypromellose type 2910 USP, titanium dioxide USP, lactose monohydrate NF, polyethylene glycol 3350 NF, triacetin USP, and FD&C Red #40. The 65 mg tablets also contain Opadry II Blue which contains: hypromellose type 2910 USP, lactose monohydrate NF, FD&C Blue #1, polyethylene glycol 3350 NF, FD&C Blue #2, titanium dioxide USP, triacetin USP, and D&C Yellow #10. The 80 mg tablets also contain Opadry II Gray which contains: hypromellose type 2910 USP, lactose monohydrate NF, polyethylene glycol 3350 NF, FD&C Blue #2, FD&C Red #40, titanium dioxide USP, triacetin USP, and FD&C Yellow #6. The 90 mg tablets also contain Opadry II Yellow which contains: hypromellose type 2910 USP, lactose monohydrate NF, titanium dioxide USP, iron oxide yellow NF, polyethylene glycol 3350 NF, and triacetin USP. The 105 mg tablets also contain Opadry II Purple which contains: hypromellose type 2910 USP, lactose monohydrate NF, titanium dioxide USP, D&C Red #27, polyethylene glycol 3350 NF, triacetin USP, and FD&C Blue #1. The 115 mg tablets also contain Opadry II Green which contains: hypromellose type 2910 USP, lactose monohydrate NF, D&C Yellow #10, triacetin USP, FD&C Blue #1, titanium dioxide USP, and FD&C Blue #2. The 135 mg tablets also contain Opadry II Pink which contains: hypromellose type 2910 USP, lactose monohydrate NF, titanium dioxide USP, polyethylene glycol 3350 NF, iron oxide red NF, and triacetin USP.

12 CLINICAL PHARMACOLOGY

12.1 Mechanism of Action

The mechanism of action of SOLODYN for the treatment of acne is unknown.

12.2 Pharmacodynamics

The pharmacodynamics of SOLODYN for the treatment of acne are unknown.

12.3 Pharmacokinetics

SOLODYN Tablets are not bioequivalent to non-modified release minocycline products. Based on pharmacokinetic studies in healthy adults, SOLODYN Tablets produce a delayed Tmax at 3.5–4.0 hours as compared to a non-modified release reference minocycline product (Tmax at 2.25–3 hours). At steady-state (Day 6), the mean AUC(0–24) and Cmax were 33.32 µg×hr/mL and 2.63 µg/mL for SOLODYN Tablets and 46.35 µg×hr/mL and 2.92 µg/mL for Minocin® capsules, respectively. These parameters are based on dose adjusted to 135 mg per day for both products.

A single-dose, four-way crossover study demonstrated that SOLODYN Tablets used in the study (45 mg, 90 mg, 135 mg) exhibited dose-proportional pharmacokinetics. In another single-dose, five-way crossover pharmacokinetic study, SOLODYN Tablets 55 mg, 80 mg, and 105 mg were shown to be dose-proportional to SOLODYN Tablets 90 mg and 135 mg.

When SOLODYN Tablets were administered concomitantly with a meal that included dairy products, the extent and timing of absorption of minocycline did not differ from that of administration under fasting conditions.

Minocycline is lipid soluble and distributes into the skin and sebum.

13 NONCLINICAL TOXICOLOGY

13.1 Carcinogenesis, Mutagenesis, Impairment of Fertility

Carcinogenesis—Long-term animal studies have not been performed to evaluate the carcinogenic potential of minocycline. A structurally related compound, oxytetracycline, was found to produce adrenal and pituitary tumors in rats.

Mutagenesis—Minocycline was not mutagenic in vitro in a bacterial reverse mutation assay (Ames test) or CHO/HGPRT mammalian cell assay in the presence or absence of metabolic activation. Minocycline was not clastogenic in vitro using human peripheral blood lymphocytes or in vivo in a mouse micronucleus test.

Impairment of Fertility—Male and female reproductive performance in rats was unaffected by oral doses of minocycline of up to 300 mg/kg/day (which resulted in up to approximately 40 times the level of systemic exposure to minocycline observed in patients as a result of use of SOLODYN). However, oral administration of 100 or 300 mg/kg/day of minocycline to male rats (resulting in approximately 15 to 40 times the level of systemic exposure to minocycline observed in patients as a result of use of SOLODYN) adversely affected spermatogenesis. Effects observed at 300 mg/kg/day included a reduced number of sperm cells per gram of epididymis, an apparent reduction in the percentage of sperm that were motile, and (at 100 and 300 mg/kg/day) increased numbers of morphologically abnormal sperm cells. Morphological abnormalities observed in sperm samples included absent heads, misshapen heads, and abnormal flagella.

Limited human studies suggest that minocycline may have a deleterious effect on spermatogenesis.

SOLODYN should not be used by individuals of either gender who are attempting to conceive a child.

14 CLINICAL STUDIES

The safety and efficacy of SOLODYN in the treatment of inflammatory lesions of non-nodular moderate to severe acne vulgaris was assessed in two 12-week, multi-center, randomized, double-blind, placebo-controlled, studies in subjects ≥ 12 years. The mean age of subjects was 20 years and subjects were from the following racial groups: White (73%), Hispanic (13%), Black (11%), Asian/Pacific Islander (2%), and Other (2%).

In two efficacy and safety trials, a total of 924 subjects with non-nodular moderate to severe acne vulgaris received SOLODYN or placebo for a total of 12 weeks, according to the following dose assignments.

Table 3: Clinical Studies Dosing Table
Subject's Weight (lbs.) | Subject's Weight (kg) | Available Caplet Strength (mg) | Actual mg/kg Dose
99 – 131 | 45 – 59 | 45 | 1 – 0.76
132 – 199 | 60 – 90 | 90 | 1.5 – 1
200 – 300 | 91 – 136 | 135 | 1.48 – 0.99

The two primary efficacy endpoints were:

1) Mean percent change in inflammatory lesion counts from Baseline to 12 weeks.
2) Percentage of subjects with an Evaluator's Global Severity Assessment (EGSA) of clear or almost clear at 12 weeks.
  Efficacy results are presented in Table 4.

Table 4: Efficacy Results at Week 12
 | Study 1 |  | Study 2
 | SOLODYN (1 mg/kg) N = 300 | Placebo N = 151 | SOLODYN (1 mg/kg) N = 315 | Placebo N = 158
Mean Percent Improvement in Inflammatory Lesions | 43.1% | 31.7% | 45.8% | 30.8%
No. (%) of Subjects Clear or Almost Clear on the EGSA | 52 (17.3%) | 12 (7.9%) | 50 (15.9%) | 15 (9.5%)

SOLODYN did not demonstrate any effect on non-inflammatory lesions (benefit or worsening).

16 HOW SUPPLIED/STORAGE AND HANDLING

16.1 How Supplied

SOLODYN (minocycline HCl, USP) Extended Release Tablets are supplied as aqueous film coated tablets containing minocycline hydrochloride equivalent to 80 mg minocycline, are supplied as follows.

The 80 mg extended release tablets are gray, unscored, coated, and debossed with "DYN-080" on one side. Each tablet contains minocycline hydrochloride equivalent to 80 mg minocycline, supplied as follows:

NDC 54868-6285-0 | Bottle of 30

16.2 Storage

Store at 25°C (77°F); excursions are permitted to 15°–30°C (59°–86°F) [See USP Controlled Room Temperature].

16.3 Handling

Keep out of reach of children.

Protect from light, moisture, and excessive heat.

Dispense in tight, light-resistant container with child-resistant closure.

17 PATIENT COUNSELING INFORMATION

[See FDA-approved patient labeling (Patient Information)]

Patients taking SOLODYN (minocycline HCl, USP) Extended Release Tablets should receive the following information and instructions:

- SOLODYN should not be used by pregnant women or women attempting to conceive a child [see Use in Specific Populations (8.1), Nonclinical Toxicology (13.1)].
- It is recommended that SOLODYN not be used by men who are attempting to father a child [see Nonclinical Toxicology (13.1)].
- Patients should be advised that pseudomembranous colitis can occur with minocycline therapy. If patients develop watery or bloody stools, they should seek medical attention.
- Patients should be counseled about the possibility of hepatotoxicity. Patients should seek medical advice if they experience symptoms which can include loss of appetite, tiredness, diarrhea, skin turning yellow, bleeding easily, confusion, and sleepiness.
- Patients who experience central nervous system symptoms [see Warnings and Precautions (5.5)] should be cautioned about driving vehicles or using hazardous machinery while on minocycline therapy. Patients should seek medical help for persistent headaches or blurred vision.
- Concurrent use of tetracycline may render oral contraceptives less effective [see Drug Interactions (7.5)].
- Autoimmune syndromes, including drug-induced lupus-like syndrome, autoimmune hepatitis, vasculitis and serum sickness have been observed with tetracycline-class drugs, including minocycline. Symptoms may be manifested by arthralgia, fever, rash and malaise. Patients who experience such symptoms should be cautioned to stop the drug immediately and seek medical help.
- Patients should be counseled about discoloration of skin, scars, teeth or gums that can arise from minocycline therapy.
- Photosensitivity manifested by an exaggerated sunburn reaction has been observed in some individuals taking tetracyclines, including minocycline. Patients should minimize or avoid exposure to natural or artificial sunlight (tanning beds or UVA/B treatment) while using minocycline. If patients need to be outdoors while using minocycline, they should wear loose-fitting clothes that protect skin from sun exposure and discuss other sun protection measures with their physician. Treatment should be discontinued at the first evidence of skin erythema.
- SOLODYN should be taken exactly as directed. Skipping doses or not completing the full course of therapy may decrease the effectiveness of the current treatment course and increase the likelihood that bacteria will develop resistance and will not be treatable by other antibacterial drugs in the future.
- Patients should be advised to swallow SOLODYN Tablets whole and not to chew, crush, or split the tablets.

Patient Information
SOLODYN® (SO-lo-dīn)
(minocycline HCl)
Extended Release Tablets

Read this Patient Information leaflet that comes with SOLODYN before you start taking it and each time you get a refill. There may be new information. This leaflet does not take the place of talking with your doctor about your condition or treatment.

What is SOLODYN?

SOLODYN is a tetracycline-class drug. SOLODYN is prescription medicine used to treat pimples and red bumps (non-nodular inflammatory lesions) that happen with moderate to severe acne vulgaris in people 12 years and older. SOLODYN is not effective for acne that is not red-looking (this means acne that is not inflammatory).

It is not known if SOLODYN is:

- safe for use longer than 12 weeks.
- safe and effective for the treatment of infections.
- safe and effective in children under the age of 12 years.

Who should not take SOLODYN?

Do not take SOLODYN if you are allergic to tetracycline-class drugs. Ask your doctor or pharmacist for a list of these medicines if you are not sure.

What should I tell my doctor before taking SOLODYN?

Before you take SOLODYN, tell your doctor if you:

- have kidney problems. Your doctor may prescribe a lower dose of medicine for you.
- have liver problems.
- have diarrhea or watery stools.
- have vision problems.
- plan to have surgery with general anesthesia.
- have any other medical conditions.
- are a male, and you and your female partner are trying to conceive a baby. You should not take SOLODYN\.
- are pregnant or plan to become pregnant. SOLODYN may harm your unborn baby. Taking SOLODYN while you are pregnant may cause serious side effects on the growth of bone and teeth of your baby. Talk to your doctor before taking SOLODYN if you plan to become pregnant, or if you are already taking SOLODYN and plan to become pregnant. Stop taking SOLODYN and call your doctor right away if you become pregnant while taking SOLODYN.
- are breastfeeding or plan to breastfeed. SOLODYN passes into your milk and may harm your baby. You and your doctor should decide if you will take SOLODYN or breastfeed. You should not do both.

Tell your doctor about all the other medicines you take including prescription and nonprescription medicines, vitamins and herbal supplements. SOLODYN® may affect the way other medicines work, and other medicines may affect how SOLODYN® works.

Especially tell your doctor if you take:

- birth control pills. SOLODYN® may make your birth control pills less effective. You could become pregnant. You should use a second form of birth control while taking SOLODYN®.
- a blood thinner medicine.
- a penicillin antibiotic medicine. SOLODYN® and penicillins should not be used together.
- antacids that contain aluminum, calcium, or magnesium or iron-containing products.
- an acne medicine that contains isotretinoin (Amnesteem, Claravis, Sotret). SOLODYN® and isotretinoin should not be used together.

Ask your doctor or pharmacist if you are not sure if your medicine is one that is listed above.

Know the medicines you take. Keep a list of them to show your doctor and pharmacist.

How should I take SOLODYN?

- Take SOLODYN exactly as your doctor tells you.
- Skipping doses or not taking all doses of SOLODYN may:
  - make the treatment not work as well.
  - increase the chance that the bacteria will become resistant to SOLODYN.
- SOLODYN can be taken with or without food. Taking SOLODYN with food may lower your chances of getting irritation or ulcers in your esophagus. Your esophagus is the tube that connects your mouth to your stomach.
- Swallow SOLODYN Tablets whole. Do not chew, crush, or split the tablets.

If you take too much SOLODYN, call your doctor or poison control center right away. Your doctor may do blood tests to check you for side effects during treatment with SOLODYN.

What should I avoid while taking SOLODYN?

- Avoid sunlight, sunlamps, and tanning beds. SOLODYN can make your skin sensitive to the sun and the light from sunlamps and tanning beds. You could get severe sunburn.
- Protect your skin while out in sunlight.
- You should not drive or operate dangerous machinery until you know how SOLODYN affects you. SOLODYN may cause you to feel dizzy or lightheaded, or have a spinning feeling (vertigo).

What are possible side effects of SOLODYN?

SOLODYN may cause serious side effects, including:

- Harm to an unborn baby. See "What should I tell my doctor before taking SOLODYN?"
- Permanent teeth discoloration. SOLODYN may permanently turn a baby or child's teeth yellow-grey-brown during tooth development. SOLODYN should not be used during tooth development. Tooth development happens in the last half of pregnancy, and from birth to 8 years of age. See "What should I tell my doctor before taking SOLODYN?"
- Intestine infection (pseudomembranous colitis). Pseudomembranous colitis can happen with most antibiotics, including SOLODYN. Call your doctor right away if you get watery diarrhea, diarrhea that does not go away, or bloody stools.
- Serious liver problems. Stop taking SOLODYN and call your doctor right away if you get any of the following symptoms of liver problems:
  - loss of appetite
  - tiredness
  - diarrhea
  - yellowing of your skin or the whites of your eyes
  - unexplained bleeding
  - confusion
  - sleepiness
- Central nervous system effects. See "What should I avoid while taking SOLODYN?" Central nervous system effects such as light headedness, dizziness, and a spinning feeling (vertigo) may go away during your treatment with SOLODYN or if treatment is stopped.
- Benign intracranial hypertension, also called pseudotumor cerebri. This is a condition where there is high pressure in the fluid around the brain. This swelling may lead to vision changes and permanent vision loss. Stop taking SOLODYN and tell your doctor right away if you have blurred vision, vision loss, or unusual headaches.
- Immune system reactions including a lupus-like syndrome, hepatitis, and inflammation of blood or lymph vessels (vasculitis). Using SOLODYN for a long time to treat acne may cause immune system reactions. Tell your doctor right away if you get a fever, rash, joint pain, or body weakness. Your doctor may do tests to check your blood for immune system reactions.
- Serious rash and allergic reactions. SOLODYN may cause a serious rash and allergic reactions that may affect parts of your body such as your liver, lungs, kidneys and heart. Sometimes these can lead to death.
- Stop taking SOLODYN and get medical help right away if you have any of these symptoms:
  - skin rash, hives, sores in your mouth, or your skin blisters and peels
  - swelling of your face, eyes, lips, tongue, or throat
  - trouble swallowing or breathing
  - blood in your urine
  - fever, yellowing of the skin or the whites of your eyes, dark colored urine
  - pain on the right side of the stomach area (abdominal pain)
  - chest pain or abnormal heartbeats
  - swelling in your legs, ankles, and feet
  - darkening of your nails, skin, eyes, scars, teeth, and gums

The most common side effects of SOLODYN include:

- headache
- tiredness
- dizziness or spinning feeling
- itching

Call your doctor if you have a side effect that bothers you or that does not go away. Your doctor may do tests to check you for side effects during treatment with SOLODYN.

These are not all the side effects with SOLODYN. Ask your doctor or pharmacist for more information.

Call your doctor for medical advice about side effects. You may report side effects to FDA at 1-800-FDA-1088. You may also report side effects to Medicis at 1-800-900-6389.

How should I store SOLODYN?

- Store SOLODYN between 59°F to 86°F (15°C to 30°C).
- Keep SOLODYN Tablets in the container that it comes in and keep the container tightly closed.
- Keep SOLODYN Tablets dry.

Keep SOLODYN and all medicines out of the reach of children.

General information about SOLODYN

Medicines are sometimes prescribed for purposes other than those listed in the Patient Information leaflet. Do not use SOLODYN for a condition for which it was not prescribed. Do not give SOLODYN to other people, even if they have the same symptoms you have. It may harm them.

This Patient Information leaflet summarizes the most important information about SOLODYN. If you would like more information, talk to your doctor. You can ask your doctor or pharmacist for information about SOLODYN that is written for health professionals.

For more information, call 1-800-550-5115.

What are the ingredients in SOLODYN?

Active ingredient: minocycline HCl.

Inactive ingredients: lactose monohydrate, hypromellose type 2910, magnesium stearate, colloidal silicon dioxide, and carnauba wax.

The 45 mg tablets also contain Opadry II Gray which contains: lactose monohydrate, hypromellose type 2910, titanium dioxide, triacetin, and iron oxide black JPE.

The 55 mg tablets also contain Opadry II Pink which contains: hypromellose type 2910, titanium dioxide, lactose monohydrate, polyethylene glycol 3350, triacetin, and FD&C Red #40.

The 65 mg tablets also contain Opadry II Blue which contains: hypromellose type 2910, lactose monohydrate, FD&C Blue #1, polyethylene glycol 3350, FD&C Blue #2, titanium dioxide, triacetin, and D&C Yellow #10.

The 80 mg tablets also contain Opadry II Gray which contains: hypromellose type 2910, lactose monohydrate, polyethylene glycol 3350, FD&C Blue #2, FD&C Red #40, titanium dioxide, triacetin, and FD&C Yellow #6.

The 90 mg tablets also contain Opadry II Yellow which contains: hypromellose type 2910, lactose monohydrate, titanium dioxide, iron oxide yellow, polyethylene glycol 3350, and triacetin.

The 105 mg tablets also contain Opadry II Purple which contains: hypromellose type 2910, lactose monohydrate, titanium dioxide, D&C Red #27, polyethylene glycol 3350, triacetin, and FD&C Blue #1.

The 115 mg tablets also contain Opadry II Green which contains: hypromellose type 2910, lactose monohydrate NF, D&C Yellow #10, triacetin, FD&C Blue #1, titanium dioxide, FD&C Blue #2.

The 135 mg tablets also contain Opadry II Pink which contains: hypromellose type 2910, lactose monohydrate, titanium dioxide, polyethylene glycol 3350, iron oxide red, and triacetin.

SOLODYN® is manufactured by WellSpring Pharmaceutical Canada Corp. for Medicis Pharmaceutical Corporation, Scottsdale, Arizona, 85256.

This Patient Information has been approved by the U.S. Food and Drug Administration.

Revised: 03/2011

U.S. Patent 5,908,838, U.S. Patent 7,790,705 and Patents Pending [90 mg is also covered by U.S. Patents 7,541,347 and 7,544,373]

© 2010 Medicis Pharmaceutical Corporation
SOLODYN is a registered trademark of Medicis Pharmaceutical Corporation.
All other trademarks are the properties of their respective owners.

Manufactured for:
Medicis, The Dermatology Company
Scottsdale, AZ 85256
Manufactured by:
WellSpring Pharmaceutical Canada Corp.
Oakville, Ontario, CANADA L6H 1M5
N4605D

Relabeling and Repackaging by:
Physicians Total Care, Inc.
Tulsa, OK 74146

PRINCIPAL DISPLAY PANEL - 80 mg Bottle Label

Rx Only

SOLODYN®
(MINOCYCLINE HCl, USP)
EXTENDED RELEASE TABLETS

80 mg*